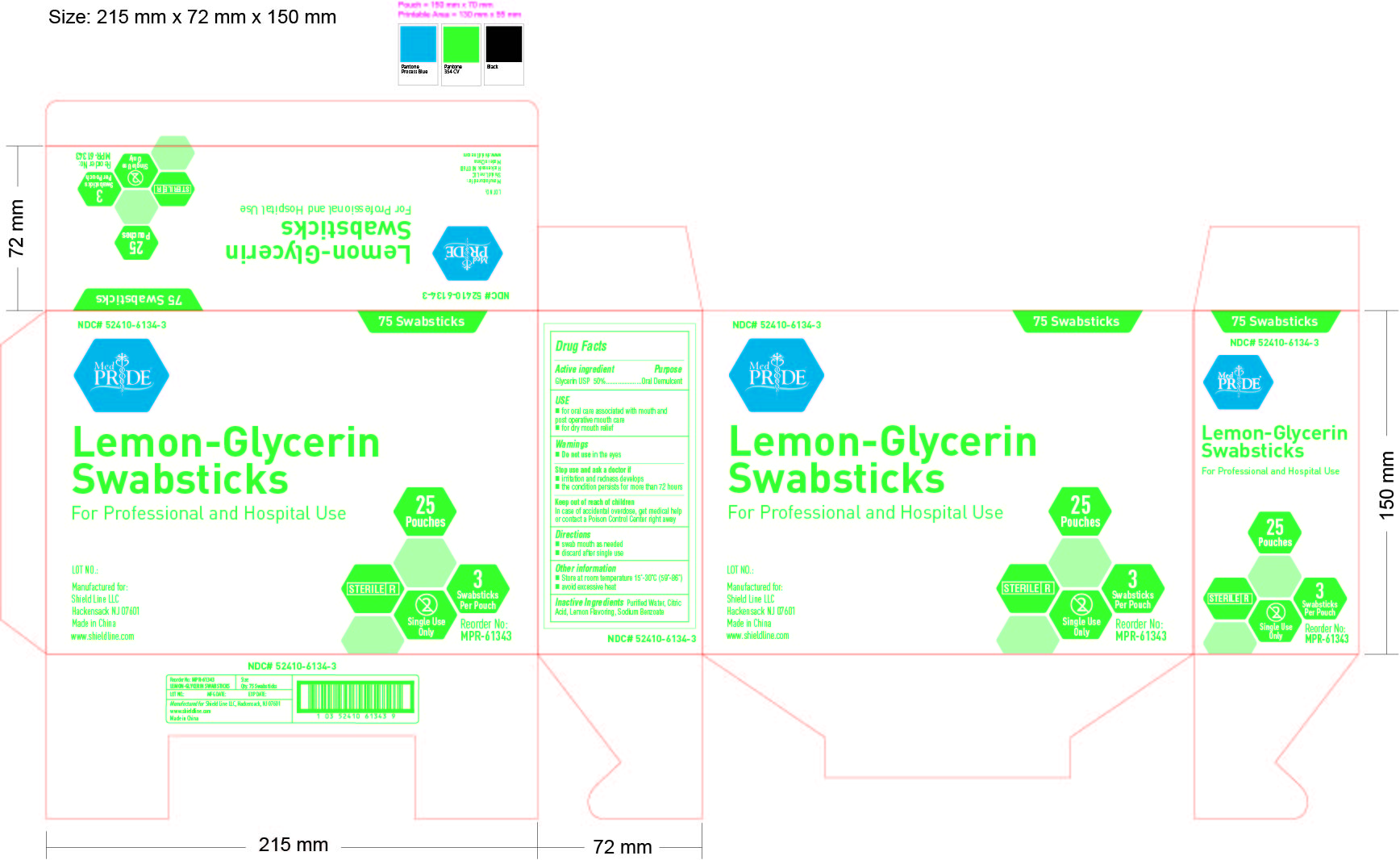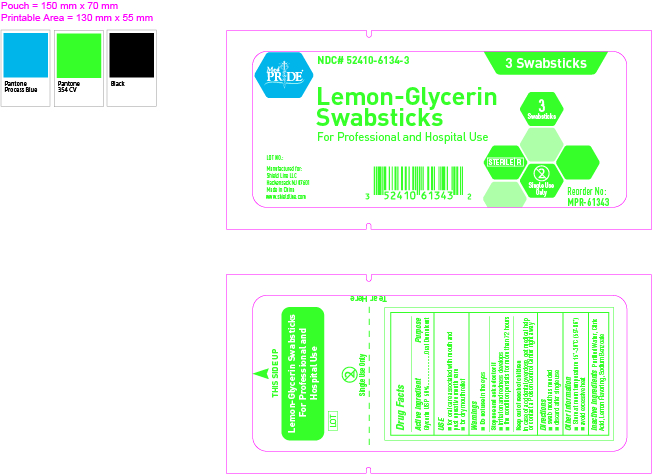 DRUG LABEL: Medpride Lemon Glycerin
NDC: 52410-6134 | Form: SWAB
Manufacturer: Shield Line LLC
Category: otc | Type: HUMAN OTC DRUG LABEL
Date: 20180808

ACTIVE INGREDIENTS: GLYCERIN 0.5 g/1 1
INACTIVE INGREDIENTS: WATER; CITRIC ACID MONOHYDRATE; SODIUM BENZOATE

Drug Facts

Active Ingredients

Glycerin USP 50%

Purpose

Oral Demulcent

USE

- for oral care associated with mouth and postoperative mouth care
- for dry mouth relief

warnings

- Do not use in the eyes

Stop Use and ask a doctor if

- If irritation and redness develops
- the condition persists more than 72 hours

KEEP OUT OF REACH OF CHILDREN

In case of accidental overdose , get medical help or contact a Poison Control Center right away

Directions

- swab mouth as needed
- discard after single use

Other Information

- Store at room temperature 15o-30o C (59o-86o F)
- avoid excessive heat

Inactive Ingredients

Purified Water, Citric Acid, Lemon Flavoring, Sodium Benzoate